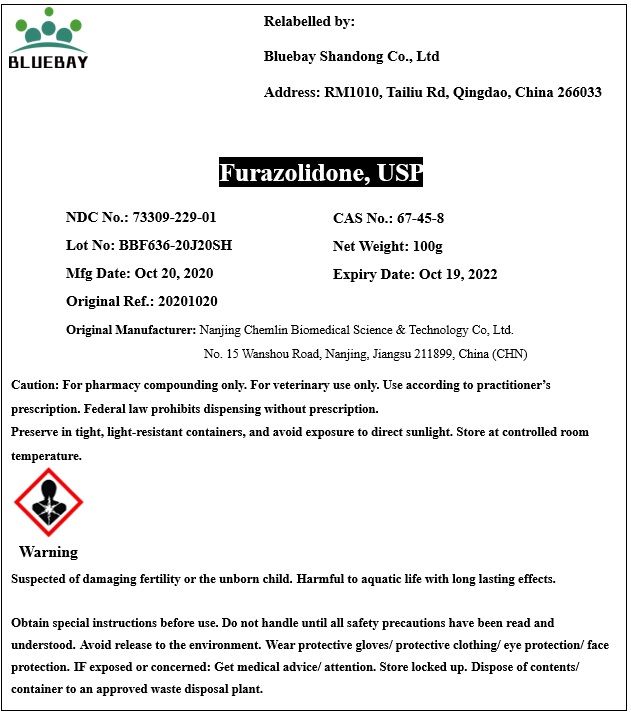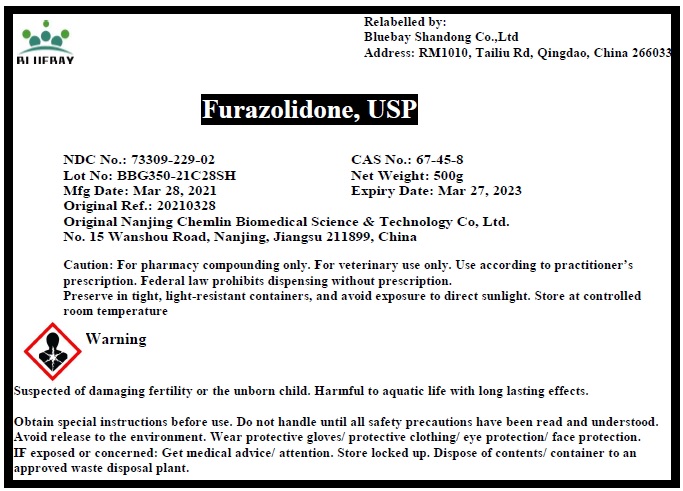 DRUG LABEL: Furazolidone
NDC: 73309-229 | Form: POWDER
Manufacturer: BLUEBAY SHANDONG CO.,LTD
Category: other | Type: BULK INGREDIENT
Date: 20210702

ACTIVE INGREDIENTS: Furazolidone 1 g/1 g

Furazolidone